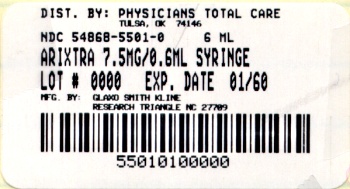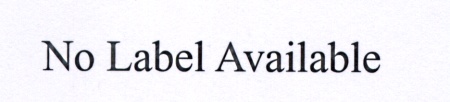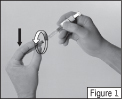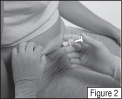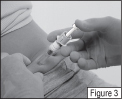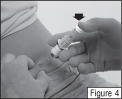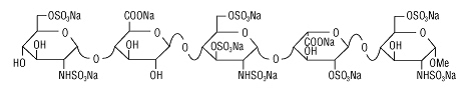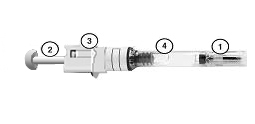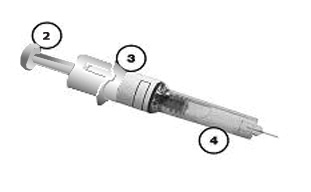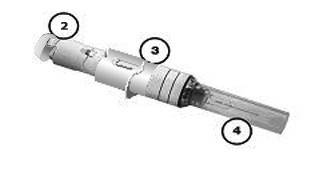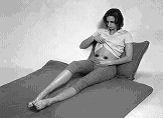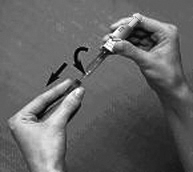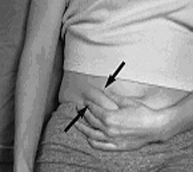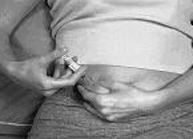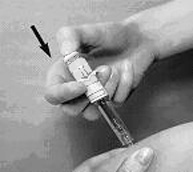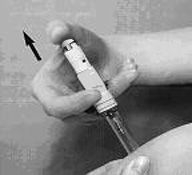 DRUG LABEL: ARIXTRA
NDC: 54868-5652 | Form: INJECTION, SOLUTION
Manufacturer: Physicians Total Care, Inc.
Category: prescription | Type: HUMAN PRESCRIPTION DRUG LABEL
Date: 20120123

ACTIVE INGREDIENTS: FONDAPARINUX SODIUM 5 mg/0.4 mL
INACTIVE INGREDIENTS: SODIUM CHLORIDE; WATER

HIGHLIGHTS OF PRESCRIBING INFORMATION

These highlights do not include all the information needed to use ARIXTRA safely and effectively. See full prescribing information for ARIXTRA.
ARIXTRA (fondaparinux sodium) Solution for subcutaneous injection
Initial U.S. Approval: 2001

WARNING: SPINAL/EPIDURAL HEMATOMAS

Epidural or spinal hematomas may occur in patients who are anticoagulated with low molecular weight heparins (LMWH), heparinoids, or fondaparinux sodium and are receiving neuraxial anesthesia or undergoing spinal puncture. These hematomas may result in long-term or permanent paralysis. Consider these risks when scheduling patients for spinal procedures. Factors that can increase the risk of developing epidural or spinal hematomas in these patients include:

● use of indwelling epidural catheters

● concomitant use of other drugs that affect hemostasis, such as non-steroidal anti-inflammatory drugs (NSAIDs), platelet inhibitors, or other anticoagulants

● a history of traumatic or repeated epidural or spinal puncture

● a history of spinal deformity or spinal surgery

Monitor patients frequently for signs and symptoms of neurologic impairment. If neurologic compromise is noted, urgent treatment is necessary.

Consider the benefit and risks before neuraxial intervention in patients anticoagulated or to be anticoagulated for thromboprophylaxis. [See Warnings and Precautions (5.5) and Drug Interactions (7).]

1 INDICATIONS AND USAGE

ARIXTRA is a Factor Xa inhibitor (anticoagulant) indicated for:

- Prophylaxis of deep vein thrombosis (DVT) in patients undergoing hip fracture surgery (including extended prophylaxis), hip replacement surgery, knee replacement surgery, or abdominal surgery. (1.1)
- Treatment of DVT or acute pulmonary embolism (PE) when administered in conjunction with warfarin. (1.2, 1.3)

2 DOSAGE AND ADMINISTRATION

- Prophylaxis of deep vein thrombosis: ARIXTRA 2.5 mg subcutaneously once daily after hemostasis has been established. The initial dose should be given no earlier than 6 to 8 hours after surgery and continued for 5 to 9 days. For patients undergoing hip fracture surgery, extended prophylaxis up to 24 additional days is recommended. (2.1, 2.2)
- Treatment of deep vein thrombosis and pulmonary embolism: ARIXTRA 5 mg (body weight <50 kg), 7.5 mg (50 to 100 kg), or 10 mg (>100 kg) subcutaneously once daily. Treatment should continue for at least 5 days until INR 2 to 3 achieved with warfarin sodium. (2.3)

Do not use as intramuscular injection. For subcutaneous use, do not mix with other injections or infusions.

3 DOSAGE FORMS AND STRENGTHS

Single-dose, prefilled syringes containing 2.5 mg, 5 mg, 7.5 mg, or 10 mg of fondaparinux. (3)

4 CONTRAINDICATIONS

ARIXTRA is contraindicated in the following conditions: (4)

- Severe renal impairment (creatinine clearance <30 mL/min) in prophylaxis or treatment of venous thromboembolism.
- Active major bleeding.
- Bacterial endocarditis.
- Thrombocytopenia associated with a positive in vitro test for anti-platelet antibody in the presence of fondaparinux sodium.
- Body weight <50 kg (venous thromboembolism prophylaxis only).

5 WARNINGS AND PRECAUTIONS

- Use with caution in patients who have conditions or are taking concomitant medications that increase risk of hemorrhage. (5.1)
- Bleeding risk is increased in renal impairment and in patients with low body weight <50 kg. (5.2, 5.3)
- Thrombocytopenia can occur with administration of ARIXTRA. (5.4)
- Periodic routine complete blood counts (including platelet counts), serum creatinine level, and stool occult blood tests are recommended (5.6)
- The packaging (needle guard) contains dry natural rubber and may cause allergic reactions in latex sensitive individuals (5.7)

6 ADVERSE REACTIONS

The most common adverse reactions associated with the use of ARIXTRA are bleeding complications. (6.1) Mild local irritation (injection site bleeding, rash, and pruritus) may occur following subcutaneous injection. (6.2)

Anemia, insomnia, increased wound drainage, hypokalemia, dizziness, hypotension, confusion, bullous eruption, hematoma, post-operative hemorrhage, and purpura may occur. (6.4)

To report SUSPECTED ADVERSE REACTIONS, contact GlaxoSmithKline at 1-888-825-5249 or FDA at 1-800-FDA-1088 or www.fda.gov/medwatch.

7 DRUG INTERACTIONS

Discontinue agents that may enhance the risk of hemorrhage prior to initiation of therapy with ARIXTRA unless essential. If co-administration is necessary, monitor patients closely for hemorrhage. (7)

8 USE IN SPECIFIC POPULATIONS

- Safety and effectiveness of ARIXTRA in pediatric patients have not been established. Because the risk for bleeding during treatment with ARIXTRA is increased in adults who weigh <50 kg, bleeding may be a particular safety concern for use of ARIXTRA in the pediatric population. (4, 5.3)
- Because elderly patients are more likely to have reduced renal function, ARIXTRA should be used with caution in these patients. (8.5)
- The risk of bleeding is increased with reduced renal or hepatic function. (8.6, 8.7)

FULL PRESCRIBING INFORMATION

WARNING: SPINAL/EPIDURAL HEMATOMAS

Epidural or spinal hematomas may occur in patients who are anticoagulated with low molecular weight heparins (LMWH), heparinoids, or fondaparinux sodium and are receiving neuraxial anesthesia or undergoing spinal puncture. These hematomas may result in long-term or permanent paralysis. Consider these risks when scheduling patients for spinal procedures. Factors that can increase the risk of developing epidural or spinal hematomas in these patients include:

● use of indwelling epidural catheters

● concomitant use of other drugs that affect hemostasis, such as non-steroidal anti-inflammatory drugs (NSAIDs), platelet inhibitors, or other anticoagulants

● a history of traumatic or repeated epidural or spinal puncture

● a history of spinal deformity or spinal surgery

Monitor patients frequently for signs and symptoms of neurologic impairment. If neurologic compromise is noted, urgent treatment is necessary.

Consider the benefit and risks before neuraxial intervention in patients anticoagulated or to be anticoagulated for thromboprophylaxis. [See Warnings and Precautions (5.5) and Drug Interactions (7).]

1 INDICATIONS AND USAGE

1.1 Prophylaxis of Deep Vein Thrombosis

ARIXTRA® is indicated for the prophylaxis of deep vein thrombosis (DVT), which may lead to pulmonary embolism (PE):

- in patients undergoing hip fracture surgery, including extended prophylaxis;
- in patients undergoing hip replacement surgery;
- in patients undergoing knee replacement surgery;
- in patients undergoing abdominal surgery who are at risk for thromboembolic complications.

1.2 Treatment of Acute Deep Vein Thrombosis

ARIXTRA is indicated for the treatment of acute deep vein thrombosis when administered in conjunction with warfarin sodium.

1.3 Treatment of Acute Pulmonary Embolism

ARIXTRA is indicated for the treatment of acute pulmonary embolism when administered in conjunction with warfarin sodium when initial therapy is administered in the hospital.

2 DOSAGE AND ADMINISTRATION

Do not mix other medications or solutions with ARIXTRA. Administer ARIXTRA only subcutaneously.

2.1 Deep Vein Thrombosis Prophylaxis Following Hip Fracture, Hip Replacement, and Knee Replacement Surgery

In patients undergoing hip fracture, hip replacement, or knee replacement surgery, the recommended dose of ARIXTRA is 2.5 mg administered by subcutaneous injection once daily after hemostasis has been established. Administer the initial dose no earlier than 6 to 8 hours after surgery. Administration of ARIXTRA earlier than 6 hours after surgery increases the risk of major bleeding. The usual duration of therapy is 5 to 9 days; up to 11 days of therapy was administered in clinical trials.

In patients undergoing hip fracture surgery, an extended prophylaxis course of up to 24 additional days is recommended. In patients undergoing hip fracture surgery, a total of 32 days (peri-operative and extended prophylaxis) was administered in clinical trials. [See Warnings and Precautions (5.6), Adverse Reactions (6), and Clinical Studies (14)].

2.2 Deep Vein Thrombosis Prophylaxis Following Abdominal Surgery

In patients undergoing abdominal surgery, the recommended dose of ARIXTRA is 2.5 mg administered by subcutaneous injection once daily after hemostasis has been established. Administer the initial dose no earlier than 6 to 8 hours after surgery. Administration of ARIXTRA earlier than 6 hours after surgery increases the risk of major bleeding. The usual duration of administration is 5 to 9 days, and up to 10 days of ARIXTRA was administered in clinical trials.

2.3 Deep Vein Thrombosis and Pulmonary Embolism Treatment

In patients with acute symptomatic DVT and in patients with acute symptomatic PE, the recommended dose of ARIXTRA is 5 mg (body weight <50 kg), 7.5 mg (body weight 50 to 100 kg), or 10 mg (body weight >100 kg) by subcutaneous injection once daily (ARIXTRA treatment regimen). Initiate concomitant treatment with warfarin sodium as soon as possible, usually within 72 hours. Continue treatment with ARIXTRA for at least 5 days and until a therapeutic oral anticoagulant effect is established (INR 2 to 3). The usual duration of administration of ARIXTRA is 5 to 9 days; up to 26 days of ARIXTRA injection was administered in clinical trials. [See Warnings and Precautions (5.6), Adverse Reactions (6), and Clinical Studies (14)].

2.4 Hepatic Impairment

No dose adjustment is recommended in patients with mild to moderate hepatic impairment, based upon single-dose pharmacokinetic data. Pharmacokinetic data are not available for patients with severe hepatic impairment. Patients with hepatic impairment may be particularly vulnerable to bleeding during ARIXTRA therapy. Observe these patients closely for signs and symptoms of bleeding. [See Clinical Pharmacology (12.4).]

2.5 Instructions for Use

ARIXTRA Injection is provided in a single-dose, prefilled syringe affixed with an automatic needle protection system. ARIXTRA is administered by subcutaneous injection. It must not be administered by intramuscular injection. ARIXTRA is intended for use under a physician’s guidance. Patients may self-inject only if their physician determines that it is appropriate and the patients are trained in subcutaneous injection techniques.

Prior to administration, visually inspect ARIXTRA to ensure the solution is clear and free of particulate matter.

To avoid the loss of drug when using the prefilled syringe, do not expel the air bubble from the syringe before the injection. Administration should be made in the fatty tissue, alternating injection sites (e.g., between the left and right anterolateral or the left and right posterolateral abdominal wall).

To administer ARIXTRA:

1. Wipe the surface of the injection site with an alcohol swab.

2. Hold the syringe with either hand and use your other hand to twist the rigid needle guard (covers the needle) counter-clockwise. Pull the rigid needle guard straight off the needle (Figure 1). Discard the needle guard.

3. Do not try to remove the air bubbles from the syringe before giving the injection.

4. Pinch a fold of skin at the injection site between your thumb and forefinger and hold it throughout the injection.

5. Hold the syringe with your thumb on the top pad of the plunger rod and your next 2 fingers on the finger grips on the syringe barrel. Pay attention to avoid sticking yourself with the exposed needle (Figure 2).

6. Insert the full length of the syringe needle perpendicularly into the skin fold held between the thumb and forefinger (Figure 3).

7. Push the plunger rod firmly with your thumb as far as it will go. This will ensure you have injected all the contents of the syringe (Figure 4).

8. When you have injected all the contents of the syringe, the plunger should be released. The plunger will then rise automatically while the needle withdraws from the skin and retracts into the security sleeve. Discard the syringe into the sharps container.

9. You will know that the syringe has worked when:

- The needle is pulled back into the security sleeve and the white safety indicator appears above the upper body.
- You may also hear or feel a soft click when the plunger rod is released fully.

3 DOSAGE FORMS AND STRENGTHS

Single-dose, prefilled syringes containing either 2.5 mg, 5 mg, 7.5 mg, or 10 mg of fondaparinux.

4 CONTRAINDICATIONS

ARIXTRA is contraindicated in the following conditions:

- Severe renal impairment (creatinine clearance [CrCl] <30 mL/min). [See Warnings and Precautions (5.2) and Use in Specific Populations (8.6).]
- Active major bleeding.
- Bacterial endocarditis.
- Thrombocytopenia associated with a positive in vitro test for anti-platelet antibody in the presence of fondaparinux sodium.
- Body weight <50 kg (venous thromboembolism [VTE] prophylaxis only) [see Warnings and Precautions (5.3)].

5 WARNINGS AND PRECAUTIONS

5.1 Hemorrhage

Use ARIXTRA with extreme caution in conditions with increased risk of hemorrhage, such as congenital or acquired bleeding disorders, active ulcerative and angiodysplastic gastrointestinal disease, hemorrhagic stroke, uncontrolled arterial hypertension, diabetic retinopathy, or shortly after brain, spinal, or ophthalmological surgery. Isolated cases of elevated aPTT temporally associated with bleeding events have been reported following administration of ARIXTRA (with or without concomitant administration of other anticoagulants) [See Adverse Reactions (6.5)].

Do not administer agents that enhance the risk of hemorrhage with ARIXTRA unless essential for the management of the underlying condition, such as vitamin K antagonists for the treatment of VTE. If co-administration is essential, closely monitor patients for signs and symptoms of bleeding.

Do not administer the initial dose of ARIXTRA earlier than 6 to 8 hours after surgery. Administration earlier than 6 hours after surgery increases risk of major bleeding [see Dosage and Administration (2) and Adverse Reactions (6.1)].

5.2 Renal Impairment and Bleeding Risk

ARIXTRA increases the risk of bleeding in patients with impaired renal function due to reduced clearance [see Clinical Pharmacology (12.4)].

The incidence of major bleeding by renal function status reported in clinical trials of patients receiving ARIXTRA for VTE surgical prophylaxis is provided in Table 1. In these patient populations, the following is recommended:

- Do not use ARIXTRA for VTE prophylaxis and treatment in patients with CrCl <30 mL/min [see Contraindications (4)].
- Use ARIXTRA with caution in patients with CrCl 30 to 50 mL/min.

Table 1. Incidence of Major Bleeding in Patients Treated With ARIXTRA by Renal Function Status for Surgical Prophylaxis and Treatment of Deep Vein Thrombosis (DVT) and Pulmonary Embolism (PE)
 |  | Degree of Renal Impairment
Population | Timing of Dose | Normal; %; (n/N) | Mild; %; (n/N) | Moderate; %; (n/N) | Severe; %; (n/N)
CrCl (mL/min) |  | ≥80 | ≥50 - <80 | ≥30 - <50 | <30
Orthopedic surgerya | Overall | 1.6%; (25/1,565) | 2.4%; (31/1,288) | 3.8%; (19/504) | 4.8%; (4/83)
 | 6-8 hours after surgery | 1.8%; (16/905) | 2.2%; (15/675) | 2.3%; (6/265) | 0%; (0/40)
Abdominal surgery | Overall | 2.1%; (13/606) | 3.6%; (22/613) | 6.7%; (12/179) | 7.1%; (1/14)
 | 6-8 hours after surgery | 2.1%; (10/467) | 3.3%; (16/481) | 5.8%; (8/137) | 7.7%; (1/13)
DVT and PE; Treatment |  | 0.4%; (4/1,132) | 1.6%; (12/733) | 2.2%; (7/318) | 7.3%; (4/55)

CrCl = creatinine clearance.

a Hip fracture, hip replacement, and knee replacement surgery prophylaxis.

Assess renal function periodically in patients receiving ARIXTRA. Discontinue the drug immediately in patients who develop severe renal impairment while on therapy. After discontinuation of ARIXTRA, its anticoagulant effects may persist for 2 to 4 days in patients with normal renal function (i.e., at least 3 to 5 half-lives). The anticoagulant effects of ARIXTRA may persist even longer in patients with renal impairment [see Clinical Pharmacology (12.4)].

5.3 Body Weight <50 Kg and Bleeding Risk

ARIXTRA increases the risk for bleeding in patients who weigh less than 50 kg, compared to patients with higher weights.

In patients who weigh less than 50 kg:

- Do not administer ARIXTRA as prophylactic therapy for patients undergoing hip fracture, hip replacement, or knee replacement surgery and abdominal surgery [see Contraindications (4)].
- Use ARIXTRA with caution in the treatment of PE and DVT.

During the randomized clinical trials of VTE prophylaxis in the peri-operative period following hip fracture, hip replacement, or knee replacement surgery and abdominal surgery, major bleeding occurred at a higher rate among patients with a body weight <50 kg compared to those with a body weight >50 kg (5.4% versus 2.1% in patients undergoing hip fracture, hip replacement, or knee replacement surgery; 5.3% versus 3.3% in patients undergoing abdominal surgery).

5.4 Thrombocytopenia

Thrombocytopenia can occur with the administration of ARIXTRA. Thrombocytopenia of any degree should be monitored closely. Discontinue ARIXTRA if the platelet count falls below 100,000/mm^3. Moderate thrombocytopenia (platelet counts between 100,000/mm^3 and 50,000/mm^3) occurred at a rate of 3.0% in patients given ARIXTRA 2.5 mg in the peri-operative hip fracture, hip replacement, or knee replacement surgery and abdominal surgery clinical trials. Severe thrombocytopenia (platelet counts less than 50,000/mm^3) occurred at a rate of 0.2% in patients given ARIXTRA 2.5 mg in these clinical trials. During extended prophylaxis, no cases of moderate or severe thrombocytopenia were reported.

Moderate thrombocytopenia occurred at a rate of 0.5% in patients given the ARIXTRA treatment regimen in the DVT and PE treatment clinical trials. Severe thrombocytopenia occurred at a rate of 0.04% in patients given the ARIXTRA treatment regimen in the DVT and PE treatment clinical trials.

Isolated occurrences of thrombocytopenia with thrombosis that manifested similar to heparin-induced thrombocytopenia have been reported with the use of ARIXTRA in postmarketing experience. [See Adverse Reactions (6.5).]

5.5 Neuraxial Anesthesia and Post-operative Indwelling Epidural Catheter Use

Spinal or epidural hematomas, which may result in long-term or permanent paralysis, can occur with the use of anticoagulants and neuraxial (spinal/epidural) anesthesia or spinal puncture. The risk of these events may be higher with post-operative use of indwelling epidural catheters or concomitant use of other drugs affecting hemostasis such as NSAIDs [see Boxed Warning]. In the postmarketing experience, epidural or spinal hematoma has been reported in association with the use of ARIXTRA by subcutaneous (SC) injection. Monitor patients undergoing these procedures for signs and symptoms of neurologic impairment. Consider the potential risks and benefits before neuraxial intervention in patients anticoagulated or who may be anticoagulated for thromboprophylaxis.

5.6 Monitoring: Laboratory Tests

Routine coagulation tests such as Prothrombin Time (PT) and Activated Partial Thromboplastin Time (aPTT) are relatively insensitive measures of the activity of ARIXTRA and international standards of heparin or LMWH are not calibrators to measure anti-Factor Xa activity of ARIXTRA. If unexpected changes in coagulation parameters or major bleeding occur during therapy with ARIXTRA, discontinue ARIXTRA. In postmarketing experience, isolated occurrences of aPTT elevations have been reported following administration of ARIXTRA [see Adverse Reactions (6.5)].

Periodic routine complete blood counts (including platelet count), serum creatinine level, and stool occult blood tests are recommended during the course of treatment with ARIXTRA.

The anti-Factor Xa activity of fondaparinux sodium can be measured by anti-Xa assay using the appropriate calibrator (fondaparinux). The activity of fondaparinux sodium is expressed in milligrams (mg) of the fondaparinux and cannot be compared with activities of heparin or low molecular weight heparins. [See Clinical Pharmacology (12.2, 12.3).]

5.7 Latex

The packaging (needle guard) of the prefilled syringe of ARIXTRA contains dry natural latex rubber that may cause allergic reactions in latex sensitive individuals.

6 ADVERSE REACTIONS

The most serious adverse reactions reported with ARIXTRA are bleeding complications and thrombocytopenia [see Warnings and Precautions (5)].

Because clinical trials are conducted under widely varying conditions, adverse reaction rates observed in the clinical trials of a drug cannot be directly compared to rates in the clinical trials of another drug and may not reflect the rates observed in practice.

The adverse reaction information below is based on data from 8,877 patients exposed to ARIXTRA in controlled trials of hip fracture, hip replacement, major knee, or abdominal surgeries, and DVT and PE treatment. These trials consisted of the following:

- 2 peri-operative dose-response trials (n = 989)
- 4 active-controlled peri-operative VTE prophylaxis trials with enoxaparin sodium (n = 3,616), an extended VTE prophylaxis trial (n = 327), and an active-controlled trial with dalteparin sodium (n = 1,425)
- a dose-response trial (n = 111) and an active-controlled trial with enoxaparin sodium in DVT treatment (n = 1,091)
- an active-controlled trial with heparin in PE treatment (n = 1,092)

6.1 Hemorrhage

During administration of ARIXTRA, the most common adverse reactions were bleeding complications [see Warnings and Precautions (5.1)].

Hip Fracture, Hip Replacement, and Knee Replacement Surgery: The rates of major bleeding events reported during the hip fracture, hip replacement, or knee replacement surgery clinical trials with ARIXTRA 2.5 mg are provided in Table 2.

Table 2. Bleeding Across Randomized, Controlled Hip Fracture, Hip Replacement, and Knee Replacement Surgery Studies
 | Peri-Operative Prophylaxis (Day 1 to Day 7 ± 1 post-surgery) |  | Extended Prophylaxis (Day 8 to Day 28 ± 2 post-surgery)
 | ARIXTRA; 2.5 mg SC; once daily; N = 3,616 | Enoxaparin Sodiuma, b; N = 3,956 | ARIXTRA; 2.5 mg SC; once daily; N = 327 | Placebo; SC once daily; N = 329
Major bleedingc | 96 (2.7%) | 75 (1.9%) | 8 (2.4%) | 2 (0.6%)
Hip fracture | 18/831 (2.2%) | 19/842 (2.3%) | 8/327 (2.4%) | 2/329 (0.6%)
Hip replacement | 67/2,268 (3.0%) | 55/2,597 (2.1%) | — | —
Knee replacement | 11/517 (2.1%) | 1/517 (0.2%) | — | —
Fatal bleeding | 0 (0.0%) | 1 (<0.1%) | 0 (0.0%) | 0 (0.0%)
Non-fatal bleeding at critical site | 0 (0.0%) | 1 (<0.1%) | 0 (0.0%) | 0 (0.0%)
Re-operation due to bleeding | 12 (0.3%) | 10 (0.3%) | 2 (0.6%) | 2 (0.6%)
BI ≥2d | 84 (2.3%) | 63 (1.6%) | 6 (1.8%) | 0 (0.0%)
Minor bleedinge | 109 (3.0%) | 116 (2.9%) | 5 (1.5%) | 2 (0.6%)

a Enoxaparin sodium dosing regimen: 30 mg every 12 hours or 40 mg once daily.

b Not approved for use in patients undergoing hip fracture surgery.

c Major bleeding was defined as clinically overt bleeding that was (1) fatal, (2) bleeding at critical site (e.g. intracranial, retroperitoneal, intraocular, pericardial, spinal, or into adrenal gland), (3) associated with re-operation at operative site, or (4) with a bleeding index (BI) ≥2.

d BI ≥2: Overt bleeding associated only with a bleeding index (BI) ≥2 calculated as [number of whole blood or packed red blood cell units transfused + [(pre-bleeding) – (post-bleeding)] hemoglobin (g/dL) values].

e Minor bleeding was defined as clinically overt bleeding that was not major.

A separate analysis of major bleeding across all randomized, controlled, peri-operative, prophylaxis clinical studies of hip fracture, hip replacement, or knee replacement surgery according to the time of the first injection of ARIXTRA after surgical closure was performed in patients who received ARIXTRA only post-operatively. In this analysis, the incidences of major bleeding were as follows: <4 hours was 4.8% (5/104), 4 to 6 hours was 2.3% (28/1,196), 6 to 8 hours was 1.9% (38/1,965). In all studies, the majority (≥75%) of the major bleeding events occurred during the first 4 days after surgery.

Abdominal Surgery: In a randomized study of patients undergoing abdominal surgery, ARIXTRA 2.5 mg once daily (n = 1,433) was compared with dalteparin 5,000 IU once daily (n = 1,425). Bleeding rates are shown in Table 3.

Table 3. Bleeding in the Abdominal Surgery Study
 | ARIXTRA; 2.5 mg SC once daily | Dalteparin Sodium; 5,000 IU SC once daily
 | N = 1,433 | N = 1,425
Major bleedinga | 49 (3.4%) | 34 (2.4%)
Fatal bleeding | 2 (0.1%) | 2 (0.1%)
Non-fatal bleeding at critical site | 0 (0.0%) | 0 (0.0%)
Other non-fatal major bleeding
Surgical site | 38 (2.7%) | 26 (1.8%)
Non-surgical site | 9 (0.6%) | 6 (0.4%)
Minor bleedingb | 31 (2.2%) | 23 (1.6%)

a Major bleeding was defined as bleeding that was (1) fatal, (2) bleeding at the surgical site leading to intervention, (3) non-surgical bleeding at a critical site (e.g. intracranial, retroperitoneal, intraocular, pericardial, spinal, or into adrenal gland), or leading to an intervention, and/or with a bleeding index (BI) ≥2.

b Minor bleeding was defined as clinically overt bleeding that was not major.

The rates of major bleeding according to the time interval following the first ARIXTRA injection were as follows: <6 hours was 3.4% (9/263) and 6 to 8 hours was 2.9% (32/1112).

Treatment of Deep Vein Thrombosis and Pulmonary Embolism: The rates of bleeding events reported during the DVT and PE clinical trials with the ARIXTRA injection treatment regimen are provided in Table 4.

Table 4. Bleedinga in Deep Vein Thrombosis and Pulmonary Embolism Treatment Studies
 | ARIXTRA; N = 2,294 | Enoxaparin Sodium; N = 1,101 | Heparin; aPTT adjusted IV; N = 1,092
Major bleedingb | 28 (1.2%) | 13 (1.2%) | 12 (1.1%)
Fatal bleeding | 3 (0.1%) | 0 (0.0%) | 1 (0.1%)
Non-fatal bleeding at a critical site | 3 (0.1%) | 0 (0.0%) | 2 (0.2%)
Intracranial bleeding | 3 (0.1%) | 0 (0.0%) | 1 (0.1%)
Retro-peritoneal bleeding | 0 (0.0%) | 0 (0.0%) | 1 (0.1%)
Other clinically overt bleedingc | 22 (1.0%) | 13 (1.2%) | 10 (0.9%)
Minor bleedingd | 70 (3.1%) | 33 (3.0%) | 57 (5.2%)

a Bleeding rates are during the study drug treatment period (approximately 7 days). Patients were also treated with vitamin K antagonists initiated within 72 hours after the first study drug administration.

b Major bleeding was defined as clinically overt: –and/or contributing to death – and/or in a critical organ including intracranial, retroperitoneal, intraocular, spinal, pericardial, or adrenal gland – and/or associated with a fall in hemoglobin level ≥2 g/dL – and/or leading to a transfusion ≥2 units of packed red blood cells or whole blood.

c Clinically overt bleeding with a 2 g/dL fall in hemoglobin and/or leading to transfusion of PRBC or whole blood ≥2 units.

d Minor bleeding was defined as clinically overt bleeding that was not major.

6.2 Local Reactions

Local irritation (injection site bleeding, rash, and pruritus) may occur following subcutaneous injection of ARIXTRA.

6.3 Elevations of Serum Aminotransferases

In the peri-operative prophylaxis randomized clinical trials of 7 ± 2 days, asymptomatic increases in aspartate (AST) and alanine (ALT) aminotransferase levels greater than 3 times the upper limit of normal were reported in 1.7% and 2.6% of patients, respectively, during treatment with ARIXTRA 2.5 mg once daily versus 3.2% and 3.9% of patients, respectively, during treatment with enoxaparin sodium 30 mg every 12 hours or 40 mg once daily enoxaparin sodium. These elevations are reversible and rarely associated with increases in bilirubin. In the extended prophylaxis clinical trial, no significant differences in AST and ALT levels between ARIXTRA 2.5 mg and placebo-treated patients were observed.

In the DVT and PE treatment clinical trials, asymptomatic increases in AST and ALT levels greater than 3 times the upper limit of normal of the laboratory reference range were reported in 0.7% and 1.3% of patients, respectively, during treatment with ARIXTRA. In comparison, these increases were reported in 4.8% and 12.3% of patients, respectively, in the DVT treatment trial during treatment with enoxaparin sodium 1 mg/kg every 12 hours and in 2.9% and 8.7% of patients, respectively, in the PE treatment trial during treatment with aPTT adjusted heparin.

Since aminotransferase determinations are important in the differential diagnosis of myocardial infarction, liver disease, and pulmonary emboli, elevations that might be caused by drugs like ARIXTRA should be interpreted with caution.

6.4 Other Adverse Reactions

Other adverse reactions that occurred during treatment with ARIXTRA in clinical trials with patients undergoing hip fracture, hip replacement, or knee replacement surgery are provided in Table 5.

Table 5. Adverse Reactions Across Randomized, Controlled, Hip Fracture Surgery, Hip Replacement Surgery, and Knee Replacement Surgery Studies
Adverse Reactions | Peri-Operative Prophylaxis (Day 1 to Day 7 ± 1 post-surgery) |  | Extended Prophylaxis (Day 8 to Day 28 ± 2 post-surgery)
Adverse Reactions | ARIXTRA; 2.5 mg SC; once daily | Enoxaparin Sodiuma, b | ARIXTRA; 2.5 mg SC; once daily | Placebo; SC once daily
 | N = 3,616 | N = 3,956 | N = 327 | N = 329
Anemia | 707 (19.6%) | 670 (16.9%) | 5 (1.5%) | 4 (1.2%)
Insomnia | 179 (5.0%) | 214 (5.4%) | 3 (0.9%) | 1 (0.3%)
Wound drainage increased | 161 (4.5%) | 184 (4.7%) | 2 (0.6%) | 0 (0.0%)
Hypokalemia | 152 (4.2%) | 164 (4.1%) | 0 (0.0%) | 0 (0.0%)
Dizziness | 131 (3.6%) | 165 (4.2%) | 2 (0.6%) | 0 (0.0%)
Purpura | 128 (3.5%) | 137 (3.5%) | 0 (0.0%) | 0 (0.0%)
Hypotension | 126 (3.5%) | 125 (3.2%) | 1 (0.3%) | 0 (0.0%)
Confusion | 113 (3.1%) | 132 (3.3%) | 4 (1.2%) | 1 (0.3%)
Bullous eruptionc | 112 (3.1%) | 102 (2.6%) | 0 (0.0%) | 1 (0.3%)
Hematoma | 103 (2.8%) | 109 (2.8%) | 7 (2.1%) | 1 (0.3%)
Post-operative hemorrhage | 85 (2.4%) | 69 (1.7%) | 2 (0.6%) | 2 (0.6%)

a Enoxaparin sodium dosing regimen: 30 mg every 12 hours or 40 mg once daily.

b Not approved for use in patients undergoing hip fracture surgery.

c Localized blister coded as bullous eruption.

Adverse reactions in the abdominal surgery study and in the VTE treatment trials generally occurred at lower rates than in the hip and knee surgery trials described above. The most common adverse reaction in the abdominal surgery trial was post-operative wound infection (4.9%), and the most common adverse reaction in the VTE treatment trials was epistaxis (1.3%).

6.5 Postmarketing Experience

The following adverse reactions have been identified during post-approval use of ARIXTRA. Because these reactions are reported voluntarily from a population of uncertain size, it is not always possible to reliably estimate their frequency or establish a causal relationship to drug exposure.

Isolated occurrences of thrombocytopenia with thrombosis that manifested similar to heparin-induced thrombocytopenia have been reported in the postmarketing experience and isolated cases of elevated aPTT temporally associated with bleeding events have been reported following administration of ARIXTRA (with or without concomitant administration of other anticoagulants) [see Warnings and Precautions (5.4)].

7 DRUG INTERACTIONS

In clinical studies performed with ARIXTRA, the concomitant use of oral anticoagulants (warfarin), platelet inhibitors (acetylsalicylic acid), NSAIDs (piroxicam), and digoxin did not significantly affect the pharmacokinetics/pharmacodynamics of fondaparinux sodium. In addition, ARIXTRA neither influenced the pharmacodynamics of warfarin, acetylsalicylic acid, piroxicam, and digoxin, nor the pharmacokinetics of digoxin at steady state.

Agents that may enhance the risk of hemorrhage should be discontinued prior to initiation of therapy with ARIXTRA unless these agents are essential. If co-administration is necessary, monitor patients closely for hemorrhage. [See Warnings and Precautions (5.1).]

In an in vitro study in human liver microsomes, inhibition of CYP2A6 hydroxylation of coumarin by fondaparinux (200 micromolar i.e., 350 mg/L) was 17 to 28%. Inhibition of the other isozymes evaluated (CYPs 1A2, 2C9, 2C19, 2D6, 3A4, and 3E1) was 0 to 16%. Since fondaparinux does not markedly inhibit CYP450s (CYP1A2, CYP2A6, CYP2C9, CYP2C19, CYP2D6, CYP2E1, or CYP3A4) in vitro, fondaparinux sodium is not expected to significantly interact with other drugs in vivo by inhibition of metabolism mediated by these isozymes.

Since fondaparinux sodium does not bind significantly to plasma proteins other than ATIII, no drug interactions by protein-binding displacement are expected.

8 USE IN SPECIFIC POPULATIONS

8.1 Pregnancy

Pregnancy Category B. Reproduction studies have been performed in pregnant rats at subcutaneous doses up to 10 mg/kg/day (about 32 times the recommended human dose based on body surface area) and pregnant rabbits at subcutaneous doses up to 10 mg/kg/day (about 65 times the recommended human dose based on body surface area) and have revealed no evidence of impaired fertility or harm to the fetus due to fondaparinux sodium. There are, however, no adequate and well-controlled studies in pregnant women. Because animal reproduction studies are not always predictive of human response, ARIXTRA should be used during pregnancy only if clearly needed.

8.3 Nursing Mothers

Fondaparinux sodium was found to be excreted in the milk of lactating rats. However, it is not known whether this drug is excreted in human milk. Because many drugs are excreted in human milk, caution should be exercised when ARIXTRA is administered to a nursing mother.

8.4 Pediatric Use

Safety and effectiveness of ARIXTRA in pediatric patients have not been established. Because risk for bleeding during treatment with ARIXTRA is increased in adults who weigh <50 kg, bleeding may be a particular safety concern for use of ARIXTRA in the pediatric population [see Warnings and Precautions (5.3)].

8.5 Geriatric Use

In clinical trials the efficacy of ARIXTRA in the elderly (65 years or older) was similar to that seen in patients younger than 65 years; however, serious adverse events increased with age. Exercise caution when using ARIXTRA in elderly patients, paying particular attention to dosing directions and concomitant medications (especially anti-platelet medication). [See Warnings and Precautions (5.1).]

Fondaparinux sodium is substantially excreted by the kidney, and the risk of adverse reactions to ARIXTRA may be greater in patients with impaired renal function. Because elderly patients are more likely to have decreased renal function, assess renal function prior to ARIXTRA administration. [See Contraindications (4), Warnings and Precautions (5.2), and Clinical Pharmacology (12.4).]

In the peri-operative hip fracture, hip replacement, or knee replacement surgery clinical trials with patients receiving ARIXTRA 2.5 mg, serious adverse events increased with age for patients receiving ARIXTRA. The incidence of major bleeding in clinical trials of ARIXTRA by age is provided in Table 6.

Table 6. Incidence of Major Bleeding in Patients Treated With ARIXTRA by Age
 | Age
 | <65 years; % (n/N) | 65 to 74 years; % (n/N) | ≥75 years; % (n/N)
Orthopedic surgerya | 1.8% (23/1,253) | 2.2% (24/1,111) | 2.7% (33/1,277)
Extended prophylaxis | 1.9% (1/52) | 1.4% (1/71) | 2.9% (6/204)
Abdominal surgery | 3.0% (19/644) | 3.2% (16/507) | 5.0% (14/282)
DVT and PE treatment | 0.6% (7/1,151) | 1.6% (9/560) | 2.1% (12/583)

a Includes hip fracture, hip replacement, and knee replacement surgery prophylaxis.

8.6 Renal Impairment

Patients with impaired renal function are at increased risk of bleeding due to reduced clearance of ARIXTRA [see Contraindications (4) and Warnings and Precautions (5.2)]. Assess renal function periodically in patients receiving ARIXTRA. Discontinue ARIXTRA immediately in patients who develop severe renal impairment while on therapy. After discontinuation of ARIXTRA, its anticoagulant effects may persist for 2 to 4 days in patients with normal renal function (i.e., at least 3 to 5 half-lives). The anticoagulant effects of ARIXTRA may persist even longer in patients with renal impairment [see Clinical Pharmacology (12.4)].

8.7 Hepatic Impairment

Following a single, subcutaneous dose of 7.5 mg of ARIXTRA in patients with moderate hepatic impairment (Child-Pugh Category B) compared to subjects with normal liver function, changes from baseline in aPTT, PT/INR, and antithrombin III were similar in the two groups. However, a higher incidence of hemorrhage was observed in subjects with moderate hepatic impairment than in normal subjects, especially mild hematomas at the blood sampling or injection site. The pharmacokinetics of fondaparinux have not been studied in patients with severe hepatic impairment. [See Dosage and Administration (2.4) and Clinical Pharmacology (12.4).]

10 OVERDOSAGE

There is no known antidote for ARIXTRA. Overdose of ARIXTRA may lead to hemorrhagic complications. Discontinue treatment and initiate appropriate therapy if bleeding complications associated with overdosage occur.

Data obtained in patients undergoing chronic intermittent hemodialysis suggest that clearance of ARIXTRA can increase by 20% during hemodialysis.

11 DESCRIPTION

ARIXTRA (fondaparinux sodium) Injection is a sterile solution containing fondaparinux sodium. It is a synthetic and specific inhibitor of activated Factor X (Xa). Fondaparinux sodium is methyl O-2-deoxy-6-O-sulfo-2-(sulfoamino)-α-D-glucopyranosyl-(1→4)-O-β-D-glucopyra-nuronosyl-(1→4)-O-2-deoxy-3,6-di-O-sulfo-2-(sulfoamino)-α-D-glucopyranosyl-(1→4)-O-2-O-sulfo-α-L-idopyranuronosyl-(1→4)-2-deoxy-6-O-sulfo-2-(sulfoamino)-α-D-glucopyranoside, decasodium salt.

The molecular formula of fondaparinux sodium is C31H43N3Na10O49S8 and its molecular weight is 1728. The structural formula is provided below:

ARIXTRA is supplied as a sterile, preservative-free injectable solution for subcutaneous use.

Each single-dose, prefilled syringe of ARIXTRA, affixed with an automatic needle protection system, contains 2.5 mg of fondaparinux sodium in 0.5 mL, 5.0 mg of fondaparinux sodium in 0.4 mL, 7.5 mg of fondaparinux sodium in 0.6 mL, or 10.0 mg of fondaparinux sodium in 0.8 mL of an isotonic solution of sodium chloride and water for injection. The final drug product is a clear and colorless to slightly yellow liquid with a pH between 5.0 and 8.0.

12 CLINICAL PHARMACOLOGY

12.1 Mechanism of Action

The antithrombotic activity of fondaparinux sodium is the result of antithrombin III (ATIII)-mediated selective inhibition of Factor Xa. By selectively binding to ATIII, fondaparinux sodium potentiates (about 300 times) the innate neutralization of Factor Xa by ATIII. Neutralization of Factor Xa interrupts the blood coagulation cascade and thus inhibits thrombin formation and thrombus development.

Fondaparinux sodium does not inactivate thrombin (activated Factor II) and has no known effect on platelet function. At the recommended dose, fondaparinux sodium does not affect fibrinolytic activity or bleeding time.

12.2 Pharmacodynamics

Anti-Xa Activity: The pharmacodynamics/pharmacokinetics of fondaparinux sodium are derived from fondaparinux plasma concentrations quantified via anti-Factor Xa activity. Only fondaparinux can be used to calibrate the anti-Xa assay. (The international standards of heparin or LMWH are not appropriate for this use.) As a result, the activity of fondaparinux sodium is expressed as milligrams (mg) of the fondaparinux calibrator. The anti-Xa activity of the drug increases with increasing drug concentration, reaching maximum values in approximately three hours.

12.3 Pharmacokinetics

Absorption: Fondaparinux sodium administered by subcutaneous injection is rapidly and completely absorbed (absolute bioavailability is 100%). Following a single subcutaneous dose of fondaparinux sodium 2.5 mg in young male subjects, Cmax of 0.34 mg/L is reached in approximately 2 hours. In patients undergoing treatment with fondaparinux sodium injection 2.5 mg, once daily, the peak steady-state plasma concentration is, on average, 0.39 to 0.50 mg/L and is reached approximately 3 hours post-dose. In these patients, the minimum steady-state plasma concentration is 0.14 to 0.19 mg/L. In patients with symptomatic deep vein thrombosis and pulmonary embolism undergoing treatment with fondaparinux sodium injection 5 mg (body weight <50 kg), 7.5 mg (body weight 50 to 100 kg), and 10 mg (body weight >100 kg) once daily, the body-weight-adjusted doses provide similar mean steady-state peaks and minimum plasma concentrations across all body weight categories. The mean peak steady-state plasma concentration is in the range of 1.20 to 1.26 mg/L. In these patients, the mean minimum steady-state plasma concentration is in the range of 0.46 to 0.62 mg/L.

Distribution: In healthy adults, intravenously or subcutaneously administered fondaparinux sodium distributes mainly in blood and only to a minor extent in extravascular fluid as evidenced by steady state and non-steady state apparent volume of distribution of 7 to 11 L. Similar fondaparinux distribution occurs in patients undergoing elective hip surgery or hip fracture surgery. In vitro, fondaparinux sodium is highly (at least 94%) and specifically bound to antithrombin III (ATIII) and does not bind significantly to other plasma proteins (including platelet Factor 4 [PF4]) or red blood cells.

Metabolism: In vivo metabolism of fondaparinux has not been investigated since the majority of the administered dose is eliminated unchanged in urine in individuals with normal kidney function.

Elimination: In individuals with normal kidney function, fondaparinux is eliminated in urine mainly as unchanged drug. In healthy individuals up to 75 years of age, up to 77% of a single subcutaneous or intravenous fondaparinux dose is eliminated in urine as unchanged drug in 72 hours. The elimination half-life is 17 to 21 hours.

12.4 Special Populations

Renal Impairment: Fondaparinux elimination is prolonged in patients with renal impairment since the major route of elimination is urinary excretion of unchanged drug. In patients undergoing prophylaxis following elective hip surgery or hip fracture surgery, the total clearance of fondaparinux is approximately 25% lower in patients with mild renal impairment (CrCl 50 to 80 mL/min), approximately 40% lower in patients with moderate renal impairment (CrCl 30 to 50 mL/min), and approximately 55% lower in patients with severe renal impairment (<30 mL/min) compared to patients with normal renal function. A similar relationship between fondaparinux clearance and extent of renal impairment was observed in DVT treatment patients. [See Contraindications (4) and Warnings and Precautions (5.2).]

Hepatic Impairment: Following a single, subcutaneous dose of 7.5 mg of ARIXTRA in patients with moderate hepatic impairment (Child-Pugh Category B), Cmax and AUC were decreased by 22% and 39%, respectively, compared to subjects with normal liver function. The changes from baseline in pharmacodynamic parameters, such as aPTT, PT/INR, and antithrombin III, were similar in normal subjects and in patients with moderate hepatic impairment. Based on these data, no dosage adjustment is recommended in these patients. However, a higher incidence of hemorrhage was observed in subjects with moderate hepatic impairment than in normal subjects [see Use in Specific Populations (8.7)]. The pharmacokinetics of fondaparinux have not been studied in patients with severe hepatic impairment. [See Dosage and Administration (2.4).]

Pediatric: The pharmacokinetics of fondaparinux have not been investigated in pediatric patients. [See Contraindications (4), Warnings and Precautions (5.3), and Pediatric Use (8.4).]

Geriatric: Fondaparinux elimination is prolonged in patients older than 75 years. In studies evaluating fondaparinux sodium 2.5 mg prophylaxis in hip fracture surgery or elective hip surgery, the total clearance of fondaparinux was approximately 25% lower in patients older than 75 years as compared to patients younger than 65 years. A similar relationship between fondaparinux clearance and age was observed in DVT treatment patients. [See Use in Specific Populations (8.5).]

Patients Weighing Less Than 50 kg: Total clearance of fondaparinux sodium is decreased by approximately 30% in patients weighing less than 50 kg [see Dosage and Administration (2.3) and Contraindications (4)].

Gender: The pharmacokinetic properties of fondaparinux sodium are not significantly affected by gender.

Race: Pharmacokinetic differences due to race have not been studied prospectively. However, studies performed in Asian (Japanese) healthy subjects did not reveal a different pharmacokinetic profile compared to Caucasian healthy subjects. Similarly, no plasma clearance differences were observed between black and Caucasian patients undergoing orthopedic surgery.

13 NONCLINICAL TOXICOLOGY

13.1 Carcinogenesis, Mutagenesis, Impairment of Fertility

No long-term studies in animals have been performed to evaluate the carcinogenic potential of fondaparinux sodium.

Fondaparinux sodium was not genotoxic in the Ames test, the mouse lymphoma cell (L5178Y/TK+/-) forward mutation test, the human lymphocyte chromosome aberration test, the rat hepatocyte unscheduled DNA synthesis (UDS) test, or the rat micronucleus test.

At subcutaneous doses up to 10 mg/kg/day (about 32 times the recommended human dose based on body surface area), fondaparinux sodium was found to have no effect on fertility and reproductive performance of male and female rats.

14 CLINICAL STUDIES

14.1 Prophylaxis of Thromboembolic Events Following Hip Fracture Surgery

In a randomized, double-blind, clinical trial in patients undergoing hip fracture surgery, ARIXTRA 2.5 mg SC once daily was compared to enoxaparin sodium 40 mg SC once daily, which is not approved for use in patients undergoing hip fracture surgery. A total of 1,711 patients were randomized and 1,673 were treated. Patients ranged in age from 17 to 101 years (mean age 77 years) with 25% men and 75% women. Patients were 99% Caucasian, 1% other races. Patients with multiple traumas affecting more than one organ system, serum creatinine level more than 2 mg/dL (180 micromol/L), or platelet count less than 100,000/mm^3 were excluded from the trial. ARIXTRA was initiated after surgery in 88% of patients (mean 6 hours) and enoxaparin sodium was initiated after surgery in 74% of patients (mean 18 hours). For both drugs, treatment was continued for 7 ± 2 days. The primary efficacy endpoint, venous thromboembolism (VTE), was a composite of documented deep vein thrombosis (DVT) and/or documented symptomatic pulmonary embolism (PE) reported up to Day 11. The efficacy data are provided in Table 7 and demonstrate that under the conditions of the trial ARIXTRA was associated with a VTE rate of 8.3% compared with a VTE rate of 19.1% for enoxaparin sodium for a relative risk reduction of 56% (95% CI: 39%, 70%; P <0.001). Major bleeding episodes occurred in 2.2% of patients receiving ARIXTRA and 2.3% of enoxaparin sodium patients [see Adverse Reactions (6.1)].

Table 7. Efficacy of ARIXTRA in the Peri-operative Prophylaxis of Thromboembolic Events Following Hip Fracture Surgery
Endpoint | Peri-operative Prophylaxis; (Day 1 to Day 7 ± 2 post-surgery)
Endpoint | ARIXTRA; 2.5 mg SC once daily |  | Enoxaparin Sodium; 40 mg SC once daily
 | n/Na | % (95% CI) | n/Na | % (95% CI)
VTE | 52/626 | 8.3%b (6.3, 10.8) | 119/624 | 19.1% (16.1, 22.4)
All DVT | 49/624 | 7.9%b (5.9, 10.2) | 117/623 | 18.8% (15.8, 22.1)
Proximal DVT | 6/650 | 0.9%b (0.3, 2.0) | 28/646 | 4.3% (2.9, 6.2)
Symptomatic PE | 3/831 | 0.4%c (0.1, 1.1) | 3/840 | 0.4% (0.1, 1.0)

a N = all evaluable hip fracture surgery patients. Evaluable patients were those who were treated and underwent the appropriate surgery (i.e., hip fracture surgery of the upper third of the femur), with an adequate efficacy assessment up to Day 11.

b P value versus enoxaparin sodium <0.001.

c P value versus enoxaparin sodium: NS.

14.2 Extended Prophylaxis of Thromboembolic Events Following Hip Fracture Surgery

In a noncomparative, unblinded manner, 737 patients undergoing hip fracture surgery were initially treated during the peri-operative period with ARIXTRA 2.5 mg once daily for 7 ± 1 days. Eighty-one (81) of the 737 patients were not eligible for randomization into the 3-week double-blind period. Three hundred twenty-six (326) patients and 330 patients were randomized to receive ARIXTRA 2.5 mg once daily or placebo, respectively, in or out of the hospital for 21 ± 2 days. Patients ranged in age from 23 to 96 years (mean age 75 years) and were 29% men and 71% women. Patients were 99% Caucasian and 1% other races. Patients with multiple traumas affecting more than one organ system or serum creatinine level more than 2 mg/dL (180 micromol/L) were excluded from the trial. The primary efficacy endpoint, venous thromboembolism (VTE), was a composite of documented deep vein thrombosis (DVT) and/or documented symptomatic pulmonary embolism (PE) reported for up to 24 days following randomization. The efficacy data are provided in Table 8 and demonstrate that extended prophylaxis with ARIXTRA was associated with a VTE rate of 1.4% compared with a VTE rate of 35.0% for placebo for a relative risk reduction of 95.9% (95% CI = [98.7; 87.1], P <0.0001). Major bleeding rates during the 3-week extended prophylaxis period for ARIXTRA occurred in 2.4% of patients receiving ARIXTRA and 0.6% of placebo-treated patients [see Adverse Reactions (6.1)].

Table 8. Efficacy of ARIXTRA Injection in the Extended Prophylaxis of Thromboembolic Events Following Hip Fracture Surgery
Endpoint | Extended Prophylaxis; (Day 8 to Day 28 ± 2 post-surgery)
Endpoint | ARIXTRA; 2.5 mg SC once daily |  | Placebo; SC once daily
 | n/Na | % (95% CI) | n/Na | % (95% CI)
VTE | 3/208 | 1.4%b (0.3, 4.2) | 77/220 | 35.0% (28.7, 41.7)
All DVT | 3/208 | 1.4%b (0.3, 4.2) | 74/218 | 33.9% (27.7, 40.6)
Proximal DVT | 2/221 | 0.9%b (0.1, 3.2) | 35/222 | 15.8% (11.2, 21.2)
Symptomatic VTE (all) | 1/326 | 0.3%c (0.0, 1.7) | 9/330 | 2.7% (1.3, 5.1)
Symptomatic PE | 0/326 | 0.0%d (0.0, 1.1) | 3/330 | 0.9% (0.2, 2.6)

a N = all randomized evaluable hip fracture surgery patients. Evaluable patients were those who were treated in the post-randomization period, with an adequate efficacy assessment for up to 24 days following randomization.

b P value versus placebo <0.001

c P value versus placebo = 0.021.

d P value versus placebo = NS.

14.3 Prophylaxis of Thromboembolic Events Following Hip Replacement Surgery

In 2 randomized, double-blind, clinical trials in patients undergoing hip replacement surgery, ARIXTRA 2.5 mg SC once daily was compared to either enoxaparin sodium 30 mg SC every 12 hours (Study 1) or to enoxaparin sodium 40 mg SC once a day (Study 2). In Study 1, a total of 2,275 patients were randomized and 2,257 were treated. Patients ranged in age from 18 to 92 years (mean age 65 years) with 48% men and 52% women. Patients were 94% Caucasian, 4% black, <1% Asian, and 2% others. In Study 2, a total of 2,309 patients were randomized and 2,273 were treated. Patients ranged in age from 24 to 97 years (mean age 65 years) with 42% men and 58% women. Patients were 99% Caucasian, and 1% other races. Patients with serum creatinine level more than 2 mg/dL (180 micromol/L), or platelet count less than 100,000/mm^3 were excluded from both trials. In Study 1, ARIXTRA was initiated 6 ± 2 hours (mean 6.5 hours) after surgery in 92% of patients and enoxaparin sodium was initiated 12 to 24 hours (mean 20.25 hours) after surgery in 97% of patients. In Study 2, ARIXTRA was initiated 6 ± 2 hours (mean 6.25 hours) after surgery in 86% of patients and enoxaparin sodium was initiated 12 hours before surgery in 78% of patients. The first post-operative enoxaparin sodium dose was given within 12 hours after surgery in 60% of patients and 12 to 24 hours after surgery in 35% of patients with a mean of 13 hours. For both studies, both study treatments were continued for 7 ± 2 days. The efficacy data are provided in Table 9. Under the conditions of Study 1, ARIXTRA was associated with a VTE rate of 6.1% compared with a VTE rate of 8.3% for enoxaparin sodium for a relative risk reduction of 26% (95% CI: -11%, 53%; P = NS). Under the conditions of Study 2, fondaparinux sodium was associated with a VTE rate of 4.1% compared with a VTE rate of 9.2% for enoxaparin sodium for a relative risk reduction of 56% (95% CI: 33%, 73%; P <0.001). For the 2 studies combined, the major bleeding episodes occurred in 3.0% of patients receiving ARIXTRA and 2.1% of enoxaparin sodium patients [see Adverse Reactions (6.1)].

Table 9. Efficacy of ARIXTRA in the Prophylaxis of Thromboembolic Events Following Hip Replacement Surgery
Endpoint | Study 1; n/Na; % (95% CI) |  | Study 2; n/Na; % (95% CI)
Endpoint | ARIXTRA; 2.5 mg SC; once daily | Enoxaparin; Sodium; 30 mg SC; every 12 hr | ARIXTRA; 2.5 mg SC; once daily | Enoxaparin; Sodium; 40 mg SC; once daily
VTEb | 48/787; 6.1%c (4.5, 8.0) | 66/797; 8.3% (6.5, 10.4) | 37/908; 4.1%e (2.9, 5.6) | 85/919; 9.2% (7.5, 11.3)
All DVT | 44/784; 5.6%d (4.1, 7.5) | 65/796; 8.2% (6.4, 10.3) | 36/908; 4.0%e (2.8, 5.4) | 83/918; 9.0% (7.3, 11.1)
Proximal DVT | 14/816; 1.7%c (0.9, 2.9) | 10/830; 1.2% (0.6, 2.2) | 6/922; 0.7%f (0.2, 1.4) | 23/927; 2.5% (1.6, 3.7)
Symptomatic PE | 5/1,126; 0.4%c (0.1, 1.0) | 1/1,128; 0.1% (0.0, 0.5) | 2/1,129; 0.2%c (0.0, 0.6) | 2/1,123; 0.2% (0.0, 0.6)

a N = all evaluable hip replacement surgery patients. Evaluable patients were those who were treated and underwent the appropriate surgery (i.e., hip replacement surgery), with an adequate efficacy assessment up to Day 11.

b VTE was a composite of documented DVT and/or documented symptomatic PE reported up to Day 11.

c P value versus enoxaparin sodium: NS.

d P value versus enoxaparin sodium in study 1: <0.05.

e P value versus enoxaparin sodium in study 2: <0.001.

f P value versus enoxaparin sodium in study 2: <0.01.

14.4 Prophylaxis of Thromboembolic Events Following Knee Replacement Surgery

In a randomized, double-blind, clinical trial in patients undergoing knee replacement surgery (i.e., surgery requiring resection of the distal end of the femur or proximal end of the tibia), ARIXTRA 2.5 mg SC once daily was compared to enoxaparin sodium 30 mg SC every 12 hours. A total of 1,049 patients were randomized and 1,034 were treated. Patients ranged in age from 19 to 94 years (mean age 68 years) with 41% men and 59% women. Patients were 88% Caucasian, 8% black, <1% Asian, and 3% others. Patients with serum creatinine level more than 2 mg/dL (180 micromol/L), or platelet count less than 100,000/mm^3 were excluded from the trial. ARIXTRA was initiated 6 ± 2 hours (mean 6.25 hours) after surgery in 94% of patients, and enoxaparin sodium was initiated 12 to 24 hours (mean 21 hours) after surgery in 96% of patients. For both drugs, treatment was continued for 7 ± 2 days. The efficacy data are provided in Table 10 and demonstrate that under the conditions of the trial, ARIXTRA was associated with a VTE rate of 12.5% compared with a VTE rate of 27.8% for enoxaparin sodium for a relative risk reduction of 55% (95% CI: 36%, 70%; P <0.001). Major bleeding episodes occurred in 2.1% of patients receiving ARIXTRA and 0.2% of enoxaparin sodium patients [see Adverse Reactions (6.1)].

Table 10. Efficacy of ARIXTRA in the Prophylaxis of Thromboembolic Events Following Knee Replacement Surgery
Endpoint | ARIXTRA 2.5 mg SC once daily |  | Enoxaparin Sodium; 30 mg SC every 12 hours
 | n/Na | % (95% CI) | n/Na | % (95% CI)
VTEb | 45/361 | 12.5%c (9.2, 16.3) | 101/363 | 27.8% (23.3, 32.7)
All DVT | 45/361 | 12.5%c (9.2, 16.3) | 98/361 | 27.1% (22.6, 32.0)
Proximal DVT | 9/368 | 2.4%d (1.1, 4.6) | 20/372 | 5.4% (3.3, 8.2)
Symptomatic PE | 1/517 | 0.2%d (0.0, 1.1) | 4/517 | 0.8% (0.2, 2.0)

a N = all evaluable knee replacement surgery patients. Evaluable patients were those who were treated and underwent the appropriate surgery (i.e., knee replacement surgery), with an adequate efficacy assessment up to Day 11.

b VTE was a composite of documented DVT and/or documented symptomatic PE reported up to Day 11.

c P value versus enoxaparin sodium <0.001.

d P value versus enoxaparin sodium: NS.

14.5 Prophylaxis of Thromboembolic Events Following Abdominal Surgery in Patients at Risk for Thromboembolic Complications

Abdominal surgery patients at risk included the following: Those undergoing surgery under general anesthesia lasting longer than 45 minutes who are older than 60 years with or without additional risk factors; and those undergoing surgery under general anesthesia lasting longer than 45 minutes who are older than 40 years with additional risk factors. Risk factors included neoplastic disease, obesity, chronic obstructive pulmonary disease, inflammatory bowel disease, history of deep vein thrombosis (DVT) or pulmonary embolism (PE), or congestive heart failure.

In a randomized, double-blind, clinical trial in patients undergoing abdominal surgery, ARIXTRA 2.5 mg SC once daily started postoperatively was compared to dalteparin sodium 5,000 IU SC once daily, with one 2,500 IU SC preoperative injection and a 2,500 IU SC first postoperative injection. A total of 2,927 patients were randomized and 2,858 were treated. Patients ranged in age from 17 to 93 years (mean age 65 years) with 55% men and 45% women. Patients were 97% Caucasian, 1% black, 1% Asian, and 1% others. Patients with serum creatinine level more than 2 mg/dL (180 micromol/L), or platelet count less than 100,000/mm^3 were excluded from the trial. Sixty-nine percent (69%) of study patients underwent cancer-related abdominal surgery. Study treatment was continued for 7 ± 2 days. The efficacy data are provided in Table 11 and demonstrate that prophylaxis with ARIXTRA was associated with a VTE rate of 4.6% compared with a VTE rate of 6.1% for dalteparin sodium (P = NS).

Table 11. Efficacy of ARIXTRA In Prophylaxis of Thromboembolic Events Following Abdominal Surgery
Endpoint | ARIXTRA; 2.5 mg SC once daily |  | Dalteparin Sodium; 5,000 IU SC once daily
 | n/Na | % (95% CI) | n/Na | % (95% CI)
VTEb | 47/1,027 | 4.6%c (3.4, 6.0) | 62/1,021 | 6.1% (4.7, 7.7)
All DVT | 43/1,024 | 4.2% (3.1, 5.6) | 59/1,018 | 5.8% (4.4, 7.4)
Proximal DVT | 5/1,076 | 0.5% (0.2, 1.1) | 5/1,077 | 0.5% (0.2, 1.1)
Symptomatic VTE | 6/1,465 | 0.4% (0.2, 0.9) | 5/1,462 | 0.3% (0.1, 0.8)

a N = all evaluable abdominal surgery patients. Evaluable patients were those who were randomized and had an adequate efficacy assessment up to Day 10; non-treated patients and patients who did not undergo surgery did not get a VTE assessment.

b VTE was a composite of venogram positive DVT, symptomatic DVT, non-fatal PE and/or fatal PE reported up to Day 10.

c P value versus dalteparin sodium: NS.

14.6 Treatment of Deep Vein Thrombosis

In a randomized, double-blind, clinical trial in patients with a confirmed diagnosis of acute symptomatic DVT without PE, ARIXTRA 5 mg (body weight <50 kg), 7.5 mg (body weight 50 to 100 kg), or 10 mg (body weight >100 kg) SC once daily (ARIXTRA treatment regimen) was compared to enoxaparin sodium 1 mg/kg SC every 12 hours. Almost all patients started study treatment in hospital. Approximately 30% of patients in both groups were discharged home from the hospital while receiving study treatment. A total of 2,205 patients were randomized and 2,192 were treated. Patients ranged in age from 18 to 95 years (mean age 61 years) with 53% men and 47% women. Patients were 97% Caucasian, 2% black, and 1% other races. Patients with serum creatinine level more than 2 mg/dL (180 micromol/L), or platelet count less than 100,000/mm^3 were excluded from the trial. For both groups, treatment continued for at least 5 days with a treatment duration range of 7 ± 2 days, and both treatment groups received vitamin K antagonist therapy initiated within 72 hours after the first study drug administration and continued for 90 ± 7 days, with regular dose adjustments to achieve an INR of 2 to 3. The primary efficacy endpoint was confirmed, symptomatic, recurrent VTE reported up to Day 97. The efficacy data are provided in Table 12.

Table 12. Efficacy of ARIXTRA in the Treatment of Deep Vein Thrombosis (All Randomized)
Endpoint | ARIXTRA; 5, 7.5, or 10 mg SC once daily; N = 1,098 |  | Enoxaparin Sodium; 1 mg/kg SC every 12 hours; N = 1,107
 | n | % (95% CI) | n | % (95% CI)
Total VTEa | 43 | 3.9% (2.8, 5.2) | 45 | 4.1% (3.0, 5.4)
DVT only | 18 | 1.6% (1.0, 2.6) | 28 | 2.5% (1.7, 3.6)
Non-fatal PE | 20 | 1.8% (1.1, 2.8) | 12 | 1.1% (0.6, 1.9)
Fatal PE | 5 | 0.5% (0.1, 1.1) | 5 | 0.5% (0.1, 1.1)

a VTE was a composite of symptomatic recurrent non-fatal VTE or fatal PE reported up to Day 97. The 95% confidence interval for the treatment difference for total VTE was: (-1.8% to 1.5%).

During the initial treatment period, 18 (1.6%) of patients treated with fondaparinux sodium and 10 (0.9%) of patients treated with enoxaparin sodium had a VTE endpoint (95% CI for the treatment difference [fondaparinux sodium-enoxaparin sodium] for VTE rates: -0.2%; 1.7%).

14.7 Treatment of Pulmonary Embolism

In a randomized, open-label, clinical trial in patients with a confirmed diagnosis of acute symptomatic PE, with or without DVT, ARIXTRA 5 mg (body weight <50 kg), 7.5 mg (body weight 50 to 100 kg), or 10 mg (body weight >100 kg) SC once daily (ARIXTRA treatment regimen) was compared to heparin IV bolus (5,000 USP units) followed by a continuous IV infusion adjusted to maintain 1.5 to 2.5 times aPTT control value. Patients with a PE requiring thrombolysis or surgical thrombectomy were excluded from the trial. All patients started study treatment in hospital. Approximately 15% of patients were discharged home from the hospital while receiving ARIXTRA therapy. A total of 2,213 patients were randomized and 2,184 were treated. Patients ranged in age from 18 to 97 years (mean age 62 years) with 44% men and 56% women. Patients were 94% Caucasian, 5% black, and 1% other races. Patients with serum creatinine level more than 2 mg/dL (180 micromol/L), or platelet count less than 100,000/mm^3 were excluded from the trial. For both groups, treatment continued for at least 5 days with a treatment duration range 7 ± 2 days, and both treatment groups received vitamin K antagonist therapy initiated within 72 hours after the first study drug administration and continued for 90 ± 7 days, with regular dose adjustments to achieve an INR of 2 to 3. The primary efficacy endpoint was confirmed, symptomatic, recurrent VTE reported up to Day 97. The efficacy data are provided in Table 13.

Table 13. Efficacy of ARIXTRA in the Treatment of Pulmonary Embolism (All Randomized)
Endpoint | ARIXTRA; 5, 7.5, or 10 mg SC once daily; N = 1,103 |  | Heparin; aPTT adjusted IV; N = 1,110
 | n | % (95% CI) | n | % (95% CI)
Total VTEa | 42 | 3.8% (2.8, 5.1) | 56 | 5.0% (3.8, 6.5)
DVT only | 12 | 1.1% (0.6, 1.9) | 17 | 1.5% (0.9, 2.4)
Non-fatal PE | 14 | 1.3% (0.7, 2.1) | 24 | 2.2% (1.4, 3.2)
Fatal PE | 16 | 1.5% (0.8, 2.3) | 15 | 1.4% (0.8, 2.2)

a VTE was a composite of symptomatic recurrent non-fatal VTE or fatal PE reported up to Day 97. The 95% confidence interval for the treatment difference for total VTE was: (-3.0% to 0.5%).

During the initial treatment period, 12 (1.1%) of patients treated with fondaparinux sodium and 19 (1.7%) of patients treated with heparin had a VTE endpoint (95% CI for the treatment difference [fondaparinux sodium-heparin] for VTE rates: -1.6%; 0.4%).

16 HOW SUPPLIED/STORAGE AND HANDLING

ARIXTRA Injection is available in the following strengths and package sizes:

5 mg ARIXTRA in 0.4 mL single-dose prefilled syringe, affixed with a 27-gauge x ½-inch needle and an automatic needle protection system with white plunger rod.

NDC 54868-5652-0 | 10 Single Unit Syringes

7.5 mg ARIXTRA in 0.6 mL single-dose prefilled syringe, affixed with a 27-gauge x ½-inch needle and an automatic needle protection system with white plunger rod.

NDC 54868-5501-0 | 10 Single Unit Syringes

Store at 25°C (77°F); excursions permitted to 15–30°C (59–86°F).

17 PATIENT COUNSELING INFORMATION

See FDA-Approved Patient Labeling (17.2)

17.1 Patient Advice

If the patients have had neuraxial anesthesia or spinal puncture, and particularly, if they are taking concomitant NSAIDS, platelet inhibitors, or other anticoagulants, they should be informed to watch for signs and symptoms of spinal or epidural hematomas, such as tingling, numbness (especially in the lower limbs) and muscular weakness. If any of these symptoms occur, the patients should contact his or her physician immediately.

The use of aspirin and other NSAIDS may enhance the risk of hemorrhage. Their use should be discontinued prior to ARIXTRA therapy whenever possible; if co-administration is essential, the patient’s clinical and laboratory status should be closely monitored. [See Drug Interactions (7).]

If patients must self-administer ARIXTRA (e.g., if ARIXTRA is used at home), they should be advised of the following:

- ARIXTRA should be given by subcutaneous injection. Patients must be instructed in the proper technique for administration.
- As with all anticoagulants, the most important risk with ARIXTRA administration is bleeding. Patients should be counseled on signs and symptoms of possible bleeding.
- It may take them longer than usual to stop bleeding.
- They may bruise and/or bleed more easily when they are treated with ARIXTRA.
- They should report any unusual bleeding, bruising, or signs of thrombocytopenia (such as a rash of dark red spots under the skin) to their physician [see Warnings and Precautions (5.1, 5.4)].
- To tell their physicians and dentists they are taking ARIXTRA and/or any other product known to affect bleeding before any surgery is scheduled and before any new drug is taken [see Warnings and Precautions (5.1)].
- To tell their physicians and dentists of all medications they are taking, including those obtained without a prescription, such as aspirin or other NSAIDs. [See Drug Interactions (7)].

Keep out of the reach of children.

17.2 FDA-Approved Patient Labeling

Patient labeling is provided as a tear-off leaflet at the end of this full prescribing information.

ARIXTRA is a registered trademark of GlaxoSmithKline.

GlaxoSmithKline

Research Triangle Park, NC 27709

©2011, GlaxoSmithKline. All rights reserved.

February 2011

ARX:9PI

Additional barcode labeling by:
Physicians Total Care, Inc.
Tulsa, Oklahoma 74146

PHARMACIST-DETACH HERE AND GIVE INSTRUCTIONS TO PATIENT

-------------------------------------------------------------------------------------------------------------

PATIENT INFORMATION

ARIXTRA® (Ah-RIX-trah)

fondaparinux sodium injection

Read the Patient Information that comes with ARIXTRA before you start taking it and each time you get a refill. There may be new information. This information does not take the place of talking with your doctor about your medical condition or your treatment. If you have any questions about ARIXTRA, ask your doctor or pharmacist.

What is the most important information I should know about ARIXTRA?

Certain medical procedures involving the spine, such as an epidural (pain medication given through the spine), spinal anesthesia, or spinal puncture, may be used during your hospital stay. If you need any of these procedures while receiving ARIXTRA, heparins, heparinoids, or low-molecular weight heparins (anticoagulants), you may be at risk for having a blood clot (hematoma) in or around your spine. This type of clot is very serious, as it can cause long-term and possibly permanent paralysis (loss of the ability to move).

If you receive ARIXTRA after an epidural or spinal anesthetic is used, as the anesthesia for your surgery, your doctor will watch you closely for problems with feeling (sensation) and being able to move. Tell your doctor right away if you have any of these signs and symptoms, especially in your legs and feet:

- tingling
- numbness
- muscle weakness

Because the risk of bleeding may be higher, tell your doctor before taking ARIXTRA if you:

- are also taking certain other medicines that affect blood clotting such as aspirin, an NSAID (for example, ibuprofen or naproxen), clopidogrel, or warfarin sodium.
- have bleeding problems.
- had problems in the past with pain medication given through the spine.
- have had surgery to your spine.
- have a spinal deformity.

What is ARIXTRA?

ARIXTRA is a prescription medicine that “thins your blood” (also known as an anticoagulant). ARIXTRA is used to:

- help prevent blood clots from forming in patients who have had certain surgeries of the hip, knee, or the stomach area (abdominal surgery)
- treat people who have blood clots in their legs or blood clots that travel to their lungs

It is not known if ARIXTRA is safe and effective for use in children younger than 18 years of age.

Who should not take ARIXTRA?

Do not take ARIXTRA if you have:

- certain kidney problems
- active bleeding problems
- an infection in your heart
- low platelet counts and if you test positive for a certain antibody while you are taking ARIXTRA.

People who weigh less than 110 pounds (50 kg) should not use ARIXTRA to prevent blood clots from forming after surgery.

What should I tell my doctor before taking ARIXTRA?

Tell your doctor about all of your medical conditions, including if you:

- have had any bleeding problems (such as stomach ulcers)
- have had a stroke
- have had recent surgeries, including eye surgery
- have diabetic eye disease
- have kidney problems
- have uncontrolled high blood pressure
- have a latex allergy. The packaging (needle guard) for ARIXTRA contains dry natural rubber.
- are pregnant. It is not known if ARIXTRA will harm your unborn baby. If you are pregnant, talk to your doctor about the best way for you to prevent or treat blood clots.
- are breast-feeding. It is not known if ARIXTRA passes into breast milk.

Tell your doctor about all the medicines you take including prescriptions and non-prescription medicines, vitamins, and herbal supplements. Some medicines can increase your risk of bleeding. Especially tell your doctor if you take:

- aspirin
- NSAIDS (such as ibuprofen or naproxen)
- other blood thinner medicines, such as clopidogrel or warfarin

See “What is the most important information I should know about ARIXTRA?” Do not start taking any new medicines without first talking to your doctor.

Know the medicines you take. Tell all your doctors and dentist that you take ARIXTRA, especially if you need to have any kind of surgery or a dental procedure. Keep a list of your medicines and show it to all your doctors and pharmacist before you start a new medicine.

How should I take ARIXTRA?

- Take ARIXTRA exactly as prescribed by your doctor.
- ARIXTRA is given by injection under the skin (subcutaneous injection). See “How should I give an injection of ARIXTRA?”
- If your doctor tells you that you may give yourself injections of ARIXTRA at home, you will be shown how to give the injections first before you do them on your own.
- Tell your doctor if you have any bleeding or bruising while taking ARIXTRA.
- If you miss a dose of ARIXTRA, take your dose as soon as you remember. Do not take 2 doses at the same time.
- If you take too much ARIXTRA, call your doctor right away.
- Do not use ARIXTRA if:
  - the solution appears discolored (the solution should normally appear clear),
  - you see any particles in the solution, or
  - the syringe is damaged.

What are possible side effects of ARIXTRA?

ARIXTRA can cause serious side effects. See “What is the most important information I should know about ARIXTRA?”

- Severe bleeding
  Certain conditions can increase your risk for severe bleeding, including:
  -some bleeding problems
  -some gastrointestinal problems including ulcers
  -some types of strokes
  -uncontrolled high blood pressure
  -diabetic eye disease
  -soon after brain, spine, or eye surgery
  - Certain kidney problems can also increase your risk of bleeding with ARIXTRA. Your doctor may check your kidney function while you are taking ARIXTRA.
  - People undergoing surgery who weigh less than 110 pounds. See “Who should not take ARIXTRA?”
  - Low blood platelets. Low blood platelets can happen when you take ARIXTRA. Platelets are blood cells that help your blood to clot normally. Your doctor may check your platelet counts while you take ARIXTRA.
    You may bruise or bleed more easily while taking ARIXTRA, and it may take longer than usual for bleeding to stop.
    Tell your doctor if you have any of these signs or symptoms of bleeding while taking ARIXTRA.
    -any bleeding
    -bruising
    -rash of dark red spots under the skin
- Allergic reactions. See “What should I tell my doctor before taking ARIXTRA?”

Other side effects include:

- Injection site reactions. Bleeding, rash, and itching can happen at the place where you inject ARIXTRA.
- Low red blood cell counts (anemia). Your doctor may check your red blood cell counts while you are taking ARIXTRA.
- Increased liver enzyme test results. Your doctor may check your liver function while you are taking ARIXTRA.
- Sleep problems (insomnia).

These are not all the possible side effects of ARIXTRA. Call your doctor if you have any side effects that bother you or don’t go away.

Call your doctor for medical advice about side effects. You may report side effects to the FDA at 1-800-FDA-1088.

How should I store ARIXTRA?

Store ARIXTRA at room temperature 59°F to 86°F (15°C to 30°C). Do not freeze.

Safely, throw away ARIXTRA that is out of date or no longer needed.

Keep ARIXTRA and all medicines out of the reach of children.

General information about ARIXTRA

Medicines are sometimes prescribed for purposes other than those described in patient information leaflets. Do not use ARIXTRA for a condition for which it was not prescribed. Do not give ARIXTRA to other people. It may harm them.

This leaflet summarizes the most important information about ARIXTRA. If you would like more information, talk with your doctor. You can ask your doctor or pharmacist for information about ARIXTRA that is written for healthcare professionals. For more information about ARIXTRA, go to www.ARIXTRA.com or call 1-888-825-5249.

What are the ingredients in ARIXTRA?

Active Ingredient: fondaparinux sodium

Inactive Ingredients: sodium chloride and water for injection

How should I give an injection of ARIXTRA?

ARIXTRA is injected into a skin fold of the lower stomach area (abdomen). Do not inject ARIXTRA into muscle. Usually a doctor or nurse will give this injection to you. In some cases you may be taught how to do this yourself. Be sure that you read, understand, and follow the step-by-step instructions in this leaflet, on how to give yourself an injection of ARIXTRA.

Instructions for self-administration

The different parts of ARIXTRA safety syringe are:

1. Rigid needle guard

2. Plunger

3. Finger-grip

4. Security sleeve

Syringe BEFORE USE

Syringe AFTER USE

1. Wash your hands thoroughly with soap and water. Towel dry.

2. Sit or lie down in a comfortable position. Choose a spot on the lower stomach area (abdomen), at least 2 inches below your belly button (Figure A). Change (alternate) between using the left and right side of the lower abdomen for each injection. If you have any questions talk to your nurse or doctor.

Figure A.

3. Clean the injection area with an alcohol swab.

4. Remove the needle guard, by first twisting it and then pulling it in a straight line away from the body of the syringe (Figure B). Discard the needle guard.

To prevent infection, do not touch the needle or let it come in contact with any surface before the injection. A small air bubble in the syringe is normal. To be sure that you do not lose any medicine from the syringe, do not try to remove air bubbles from the syringe before giving the injection.

Figure B.

5. Gently pinch the skin that has been cleaned to make a fold. Hold the fold between the thumb and the forefinger of one hand during the entire injection (Figure C).

Figure C.

6. Hold the syringe firmly in your other hand using the finger grip. Insert the full length of the needle directly up and down (at an angle of 90°) into the skin fold (Figure D).

Figure D.

7. Inject all of the medicine in the syringe by pressing down on the plunger as far as it goes. This will activate the automatic needle protection system (Figure E).

Figure E.

8. Release the plunger. The needle will withdraw automatically from the skin, and pull back (retract) into the security sleeve where it will be locked (Figure F).

Figure F.

Follow the instructions given to you by your nurse or doctor about the right way to throw away used syringes and needles. There may be state laws about the right way to dispose of used syringes, needles, and disposal containers.

ARIXTRA is a registered trademark of GlaxoSmithKline.

GlaxoSmithKline

Research Triangle Park, NC 27709

©2011, GlaxoSmithKline. All rights reserved.

Revised: February 2011

ARX:5PIL

PACKAGE LABEL

Principal Display Panel

NDC 54868-5652-0

Arixtra®

(fondaparinux sodium) Injection

5 mg/0.4 mL

PACKAGE LABEL

Principal Display Panel

NDC 54868-5501-0

Arixtra®

(fondaparinux sodium) Injection

7.5 mg/0.6 mL

10 x 0.6 mL

Contains 10 Single Dose, Prefilled Syringes

Rx only

Single Dose, Prefilled Syringes

Affixed with an Automatic Needle Protection System

For Subcutaneous Injection

Contents: Each single dose prefilled syringe contains 7.5 mg of fondaparinux sodium in 0.6 mL of an isotonic solution of sodium chloride and water for injection.

The needle guard of the prefilled syringe of ARIXTRA contains dry natural latex rubber that may cause allergic reactions in latex sensitive individuals.

Recommended Dose: 7.5 mg subcutaneous injection, once daily. See package insert.

Storage: Store at 25oC (77oF); excursions permitted to 15oC – 30oC (59oF -86oF), (see USP Controlled Room Temperature).